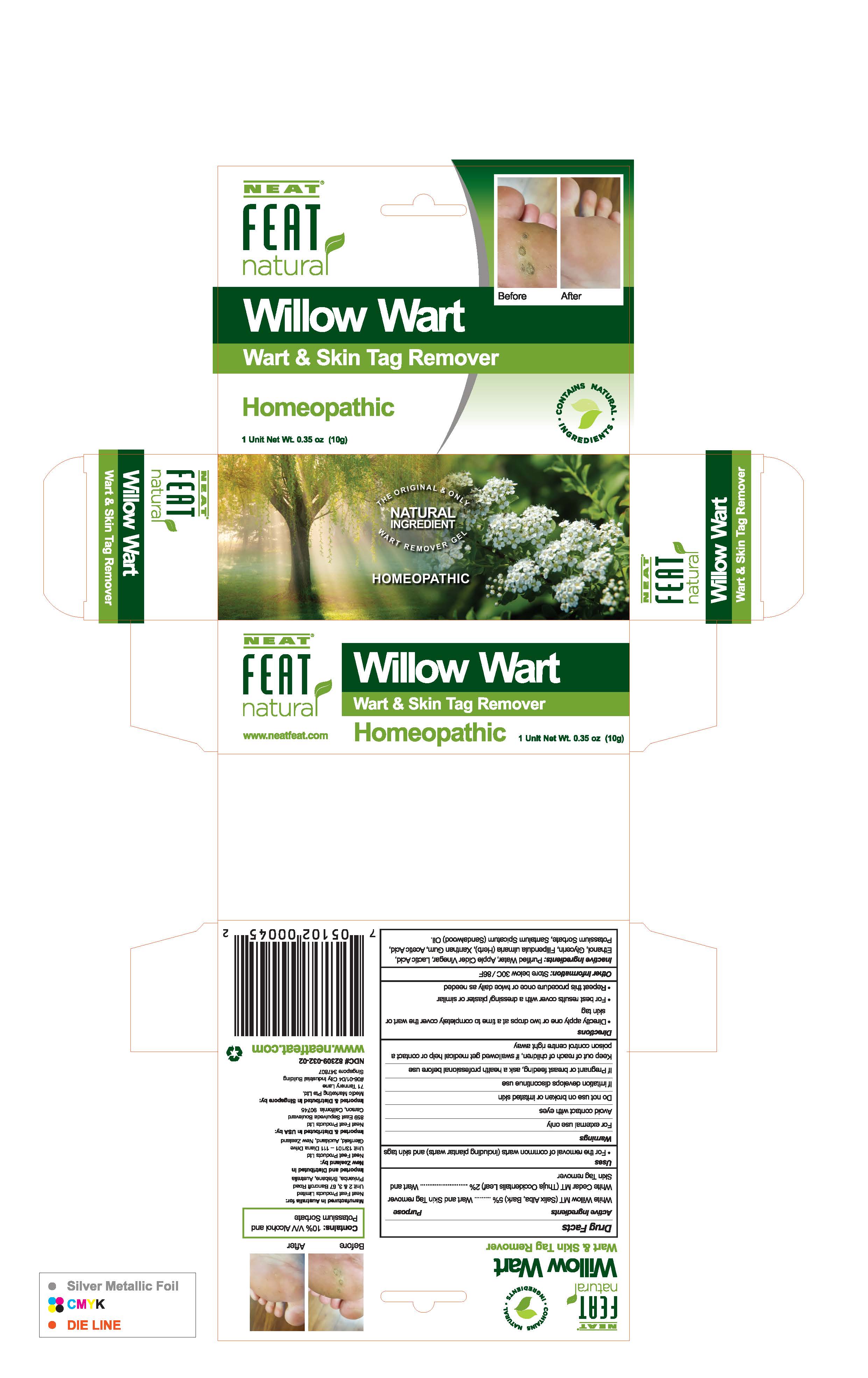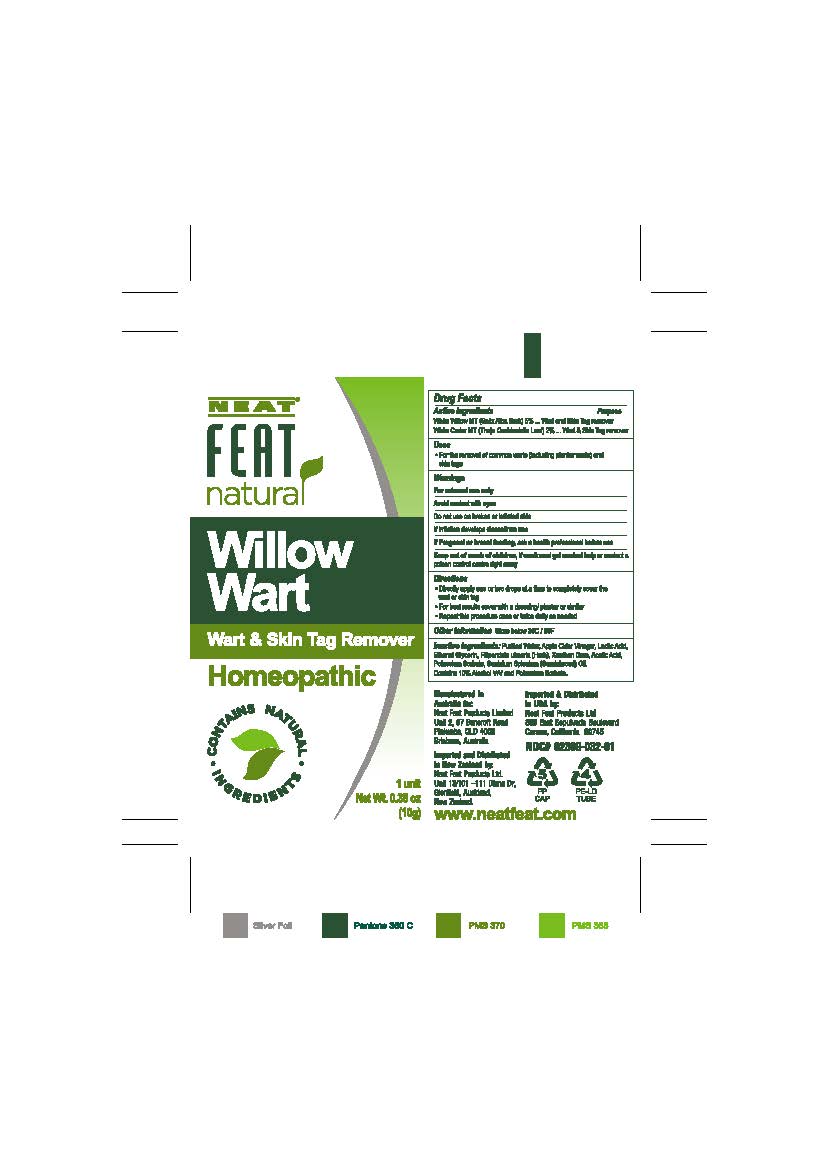 DRUG LABEL: Willow Wart
NDC: 82309-032 | Form: CREAM
Manufacturer: Tripak Pharmaceuticals
Category: homeopathic | Type: HUMAN OTC DRUG LABEL
Date: 20231218

ACTIVE INGREDIENTS: THUJA OCCIDENTALIS LEAF 0.2 g/10 g; SALIX ALBA BARK 0.5 g/10 g
INACTIVE INGREDIENTS: SANTALUM SPICATUM OIL; APPLE CIDER VINEGAR; GLYCERIN; ALCOHOL; XANTHAN GUM; WATER; LACTIC ACID; FILIPENDULA ULMARIA WHOLE; ACETIC ACID; POTASSIUM SORBATE

Willow Wart

Active Ingredients

White Willow (Salix Alba bark)

White Cedar (Thuja Occidentalis leaf)

Purpose

White Willow (Salix Alba stem and bark)..........Wart and Skin tag remover

White Cedar (Thuja Occidentalis leaf)..............Wart and Skin tag remover

Uses

- For the removal of common warts (including plantar warts) and skin tags

Warnings

For external use only

Avoid contact with eyes

Do not use on broken or irritated skin

If irritation develops discontinue use

PREGNANCY OR BREAST FEEDING

If pregnant or breast feeding, ask a health professional before use

Keep out of reach of children. If swallowed get medical help or contact a poison control centre right away.

Directions

- Directly apply one or two drops at a time to completely cover the wart or skin tag
- For best results cover with a dressing/plaster or similar
- Repeat this procedure once or twice daily as needed

Other Information

Store below 30C/86F

Inactive Ingredients

Purified Water, Apple Cider Vinegar, Alcohol, Lactic Acid, Filipendula Ulmaria Whole Plant, Glycerin, Acetic Acid, Potassium Sorbate, Santalum Spicatum (Sandalwood) Oil, Xanthan Gum

Box

82309-032-02 Box label

Tube

82309-033-01 Label